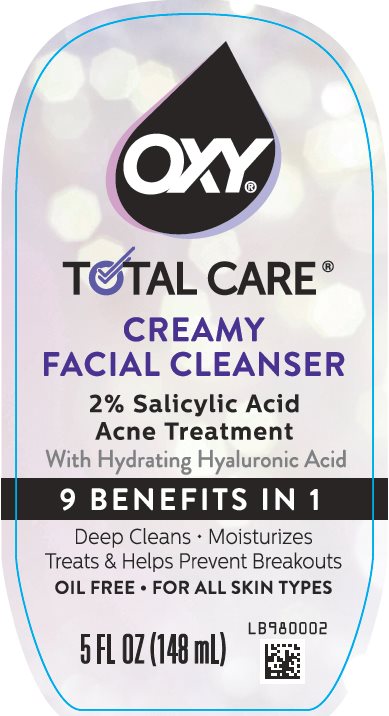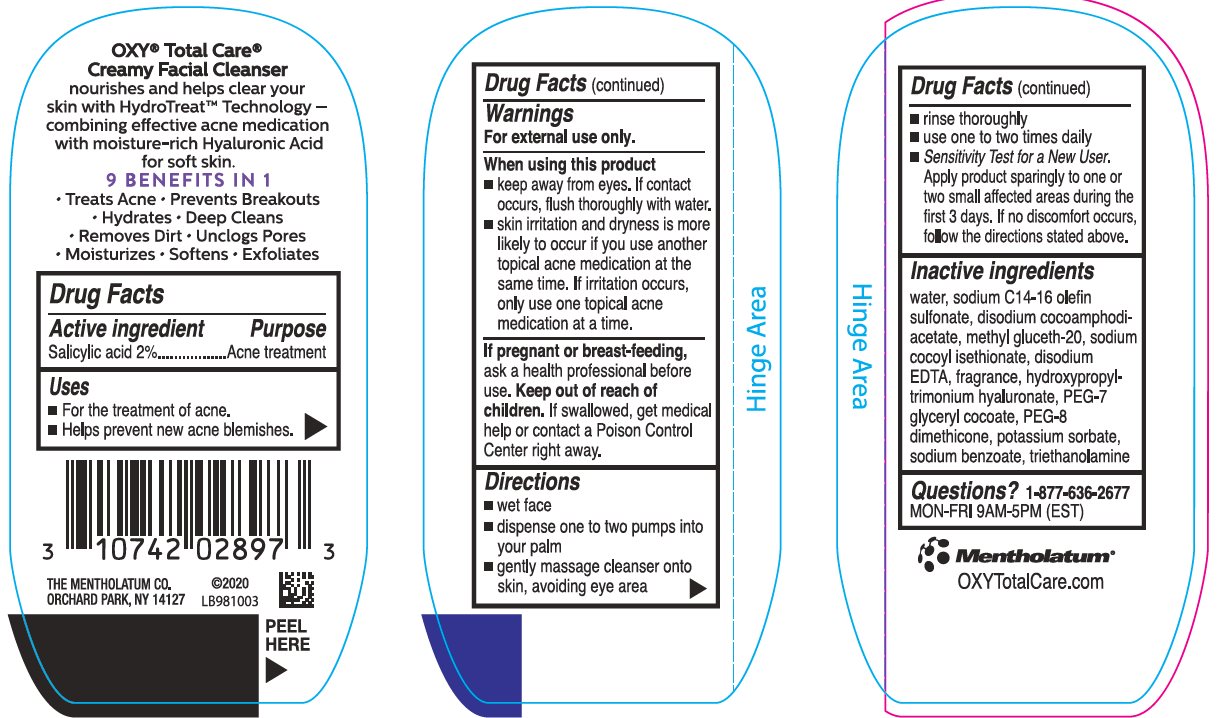 DRUG LABEL: Oxy
NDC: 10742-1316 | Form: CREAM
Manufacturer: The Mentholatum Company
Category: otc | Type: HUMAN OTC DRUG LABEL
Date: 20241213

ACTIVE INGREDIENTS: SALICYLIC ACID 20 mg/1 mL
INACTIVE INGREDIENTS: WATER; SODIUM C14-16 OLEFIN SULFONATE; DISODIUM COCOAMPHODIACETATE; METHYL GLUCETH-20; SODIUM COCOYL ISETHIONATE; EDETATE DISODIUM; HYALURONATE SODIUM; PEG-7 GLYCERYL COCOATE; PEG-8 DIMETHICONE; POTASSIUM SORBATE; SODIUM BENZOATE; TROLAMINE

Drug Facts - OXY Total Care Creamy Facial Cleanser

Active ingredient

Salicylic acid 2%

Purpose

Salicylic acid – Acne treatment

Keep Out of Reach of Children

If swallowed, get medical help or contact a Poison Control Center right away.

Uses

- For the treatment of acne.
- Helps prevent new acne blemishes.

Warnings

For external use only.

When using this product

- keep away from eyes. If contact occurs, flush thoroughly with water.
- skin irritation and dryness is more likely to occur if you use another topical acne medication at the same time. If irritation occurs, use only one topical acne medication at a time.

If pregnant or breast-feeding, ask a health professional before use.

Directions

- wet face
- dispense one to two pumps into your palm
- gently massage cleanser onto skin, avoiding eye area
- rinse thoroughly
- use one to two times daily
- Sensitivity Test for a New User. Apply product sparingly to one or two small affected areas during the first 3 days. If no discomfort occurs, follow the directions stated above.

Inactive Ingredients

water, sodium C14-16 olefin sulfonate, disodium cocoamphodiacetate, methyl gluceth-20, sodium cocoyl isethionate, disodium EDTA, fragrance, hydroxypropyltrimonium hyaluronate, PEG-7 glyceryl cocoate, PEG-8 dimethicone, potassium sorbate, sodium benzoate, triethanolamone

Questions?1-877-636-2677

MON-FRI 9AM-5PM (EST)